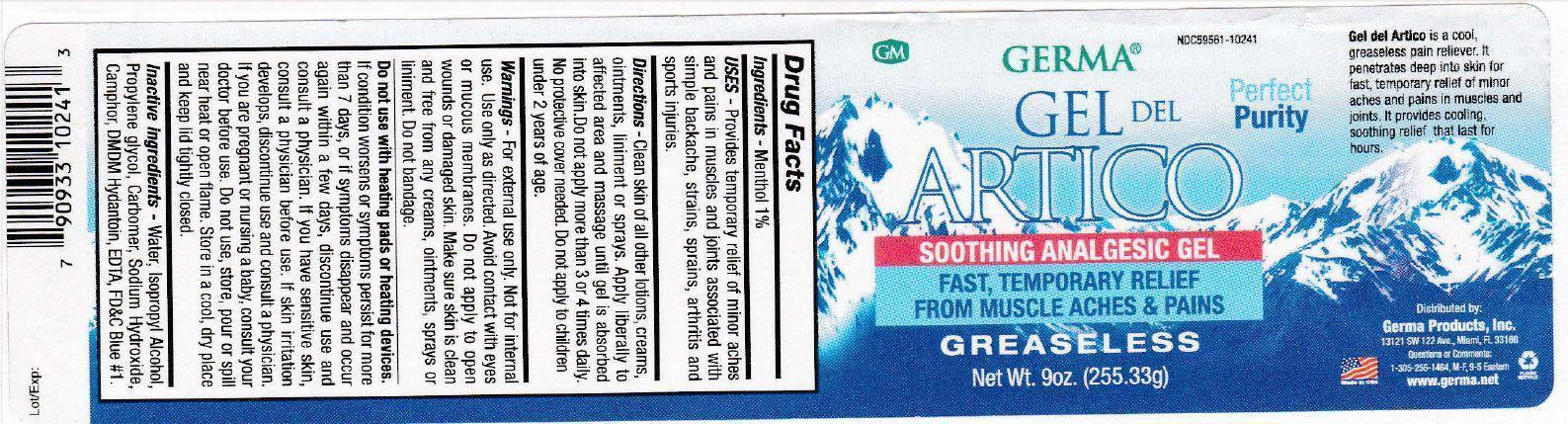 DRUG LABEL: Artico Ice
NDC: 59561-102 | Form: GEL
Manufacturer: Caribe Natural, Inc
Category: otc | Type: HUMAN OTC DRUG LABEL
Date: 20150430

ACTIVE INGREDIENTS: MENTHOL 1 g/100 g
INACTIVE INGREDIENTS: WATER; ISOPROPYL ALCOHOL; PROPYLENE GLYCOL; CARBOMER COPOLYMER TYPE A; SODIUM HYDROXIDE; CAMPHOR (NATURAL); DMDM HYDANTOIN; EDETIC ACID; FD&C BLUE NO. 1

ACTIVE INGREDIENT

Ingredients - Menthol 1%

PURPOSE

USES - Provides temporary relief of minor aches and pains in muscles and joints associated with simple backache, strains, sprains, arthritis and sports injuries.

Keep out of reach of children.

DOSAGE AND ADMINISTRATION

Gel Del Artico

Perfect Purity

Soothing Analgesic Gel

Fast, Temporary Relief from Muscle Aches & Pains

Greaseless

Gel Del Artico is a cool, greaseless pain reliever. It penetrates deep into skin for fast, temporary relief of minor aches and pains in muscles and joints. It provides cooling, soothing relief that last for hours.

WARNINGS

Warnings - For external use only. Not for internal use. Use only as directed. Avoid contact with eyes or mucous membranes. Do not apply to open wounds or damaged skin. Make sure skin is clean and free from any creams ointments, sprays or liniment. Do not bandate.

Do not use with heating pads or heating devices. If condition worsens or symptoms persist for more than 7 days, or if symptoms disappear and occur again within a few days, discontinue use and consult a physician. If you have sensitive skin, consult a physician before use. If skin irritation develops, discontinue use and consult a physician. If you are pregnant or nursing a baby, consult your doctor before use. Do not use, store, pour or spill near heat or open flame. Store in a cool, dry place and keep lid tightly closed.

INACTIVE INGREDIENT

Inactive Ingredients - water, isopropyl alcohol, propylene glycol, carbomer, sodium hydroxide, camphor, dmdm hydantoin, edta, fd&c blue #1